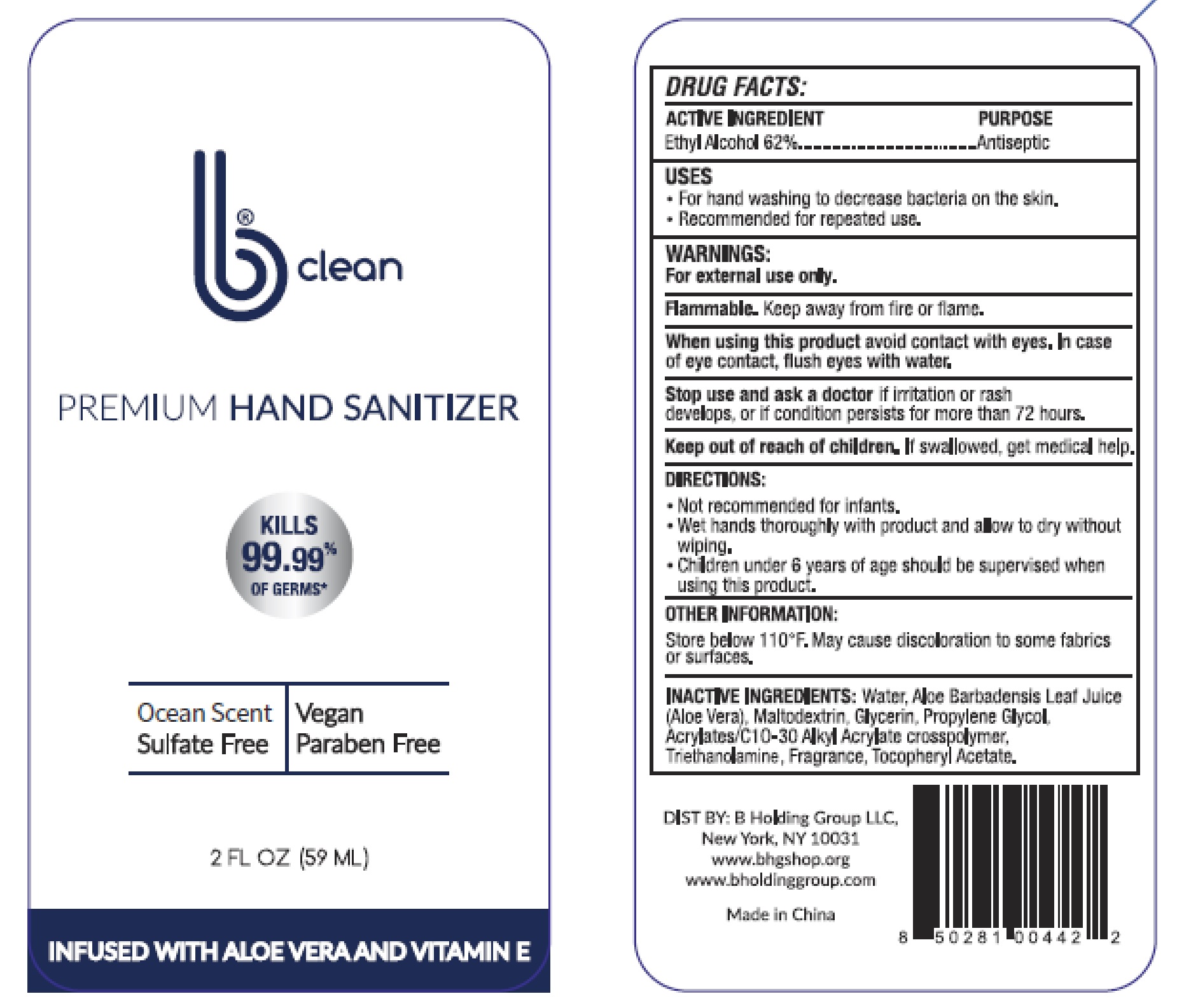 DRUG LABEL: Hand Sanitizer
NDC: 78396-002 | Form: GEL
Manufacturer: B Holding Group LLC
Category: otc | Type: HUMAN OTC DRUG LABEL
Date: 20200528

ACTIVE INGREDIENTS: ALCOHOL 62 mL/100 mL
INACTIVE INGREDIENTS: MALTODEXTRIN; PROPYLENE GLYCOL; WATER; ALOE VERA LEAF; GLYCERIN; CARBOMER INTERPOLYMER TYPE A (55000 CPS); TROLAMINE; .ALPHA.-TOCOPHEROL ACETATE

Active Ingredient
Ethyl Alcohol 62%

Purpose
Antiseptic

Uses

For hand washing to decrease bacteria on the skin.

Recommended for repeated use.

Warnings

For external use only.

Flammable. Keep away from fire or flame.

When using this product avoid contact with eyes. In case of eye contact, flush eyes with water.

Stop use and ask a doctor if irritation or rash develops, or if condition persists for more than 72 hours.

Keep out of reach of children. If swallowed, get medical help.

Directions

Not recommended for infants.

Wet hands thoroughly with product and allow to dry without wiping.

Children under 6 years of age should be supervised when using this product.

Other Information

Store below 110°F. May cause discoloration to some fabrics or surfaces.

Inactive Ingredients

Water, Aloe Barbadensis Leaf Juice, Maltodextrin,Glycerin, Propylene Glycol, Acrylates/C1O-30 Alkyl Acrylate crosspolymer, Triethanoamine, Fragrance, Tocopheryl Acetate.